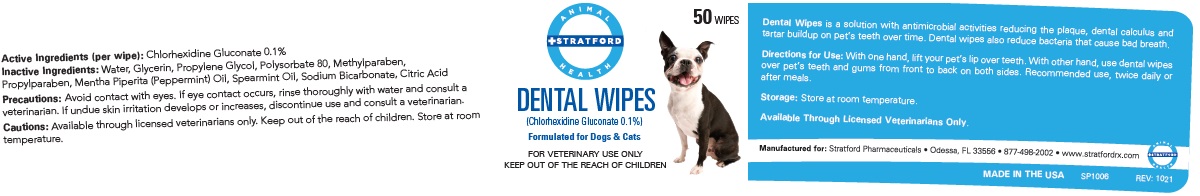 DRUG LABEL: Stratford Dental Wipes
NDC: 86069-121 | Form: CLOTH
Manufacturer: Stratford Care Usa, Inc.
Category: animal | Type: OTC ANIMAL DRUG LABEL
Date: 20220224

ACTIVE INGREDIENTS: CHLORHEXIDINE GLUCONATE 0.001 g/1 1
INACTIVE INGREDIENTS: WATER; GLYCERIN; PROPYLENE GLYCOL; POLYSORBATE 80; METHYLPARABEN; PROPYLPARABEN; PEPPERMINT OIL; SPEARMINT OIL; SODIUM BICARBONATE; CITRIC ACID MONOHYDRATE

STRATFORD DENTAL WIPES

Active Ingredients (per wipe): Chlorhexidine Gluconate 0.1%

PURPOSE

Antimicrobial

INDICATIONS AND USAGE

Dental Wipes is a solution with antimicrobial activities reducing the plaque, dental calculus and tartar buildup on pet’s teeth over time. Dental wipes also reduce bacteria that cause bad breath.

DOSAGE AND ADMINISTRATION

Directions for Use: With one hand, lift your pet’s lip over teeth. With other hand, use dental wipes over pet’s teeth and gums from front to back on both sides. Recommended use, twice daily or after meals.

Storage: Store at room temperature.

PRECAUTIONS

Precautions: Avoid contact with eyes. If eye contact occurs, rinse thoroughly with water and consult a veterinarian. If undue skin irritation develops or increases, discontinue use and consult a veterinarian.

Cautions: Keep out of the reach of children.

INACTIVE INGREDIENT

Inactive Ingredients: Water, Glycerin, Propylene Glycol, Polysorbate 80, Methylparaben, Propylparaben, Mentha Piperita (Peppermint) Oil, Spearmint Oil, Sodium Bicarbonate, Citric Acid

Formulated for Dogs & Cats

FOR VETERINARY USE ONLY

Available Through Licensed Veterinarians Only.

Manufactured for: Stratford Pharmaceuticals • Odessa, FL 33556 • 877-498-2002 • www.stratfordrx.com

MADE IN THE USA